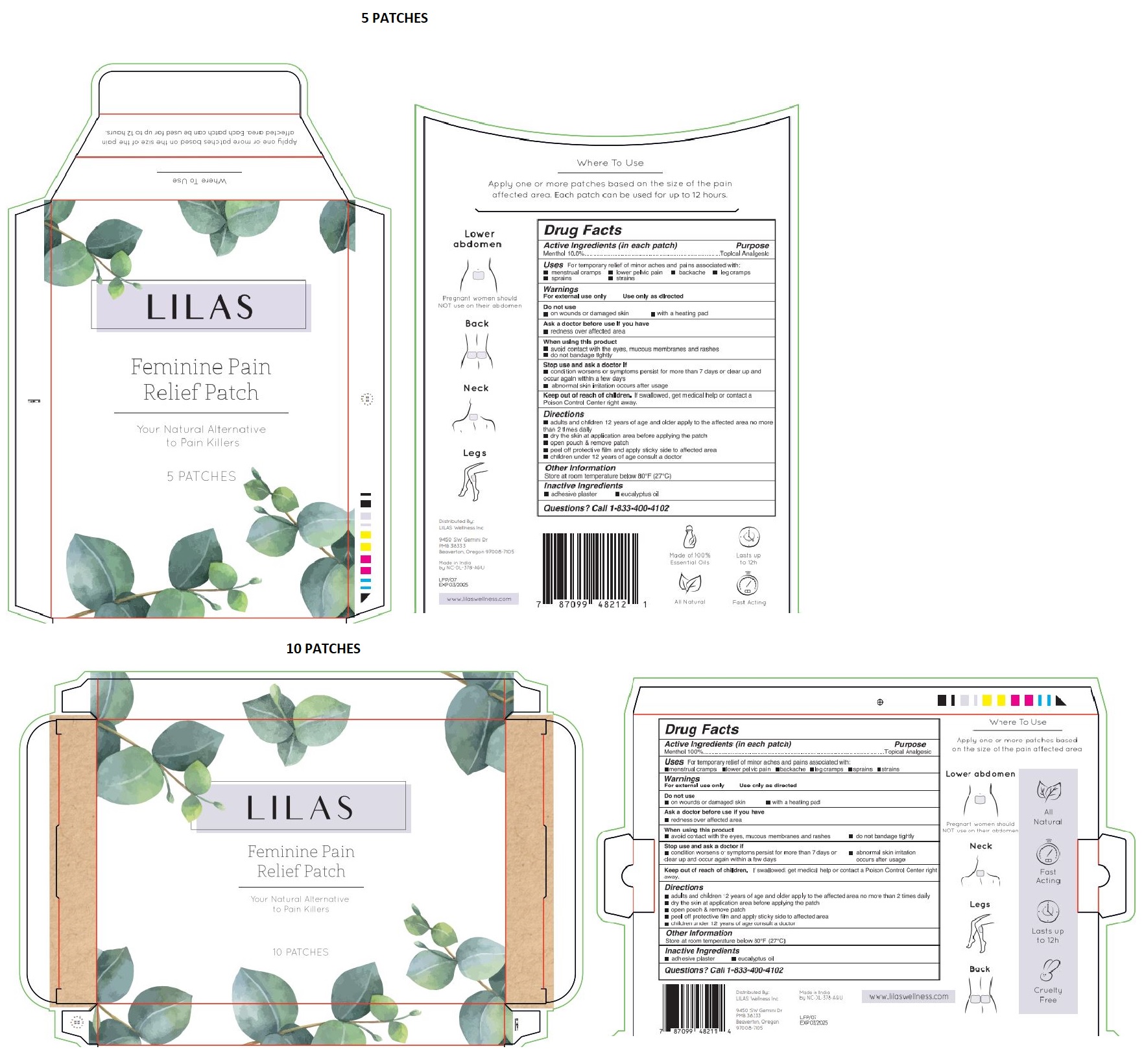 DRUG LABEL: LILAS Feminine Pain Relief Patch
NDC: 72670-001 | Form: PATCH
Manufacturer: Lilas Wellness, Inc.
Category: otc | Type: HUMAN OTC DRUG LABEL
Date: 20220620

ACTIVE INGREDIENTS: MENTHOL, UNSPECIFIED FORM 200 mg/1 1
INACTIVE INGREDIENTS: EUCALYPTUS OIL

LILAS Feminine Pain Relief Patch

Active Ingredients (In each patch)

Menthol 10.0%

Purpose

Topical Analgesic

Uses

For temporary relief of minor aches and pains associated with:
•menstrual cramps •lower pelvic pain •backache •leg cramps •sprains •strains

Warnings

For external use only Use only as directed

Do not use

• on wounds or damaged skin • with a heating pad

Ask a doctor before use if you have

• redness over affected area

When using this product

• avoid contact with the eyes, mucous membranes and rashes • do not bandage tightly

Stop use or ask a doctor if
• condition worsens or symptoms persists for more than 7 days or clear up and occur again within a few days
• abnormal skin irritation occurs after usage

Keep out of reach of children. If swallowed, get medical help or contact a Poison Control Center right away.

Directions

- adults and children 12 years of age and older apply to the affected area no more than 2 times daily
- dry the skin at application area before applying the patch
- open pouch & remove patch
- peel of protective film and apply sticky side to affected area
- children under 12 years of age consult a doctor

Other Information

Store at room temperature below 80°F (27ºC)

Inactive Ingredients

• adhesive plaster • eucalyptus oil

Questions?

Call 1-833-400-4102

Your Natural Alternative to Pain Killers

Where To Use
Apply one or more patches based on the size of the pain affected area. Each patch can be used for up to 12 hours.

Pregnant women should NOT use on their abdomen

Neck

Legs

Back

Made of 100% Essential Oils

All Natural

Fast Acting

Lasts up to 12h

Cruelty Free

Distributed By:
LILAS Wellness Inc

9450 SW Gemini Dr
PMB 38333
Beaverton, Oregon
97008-7105

Made in India
by NC-DL-378-A&U

www.lilaswellness.com